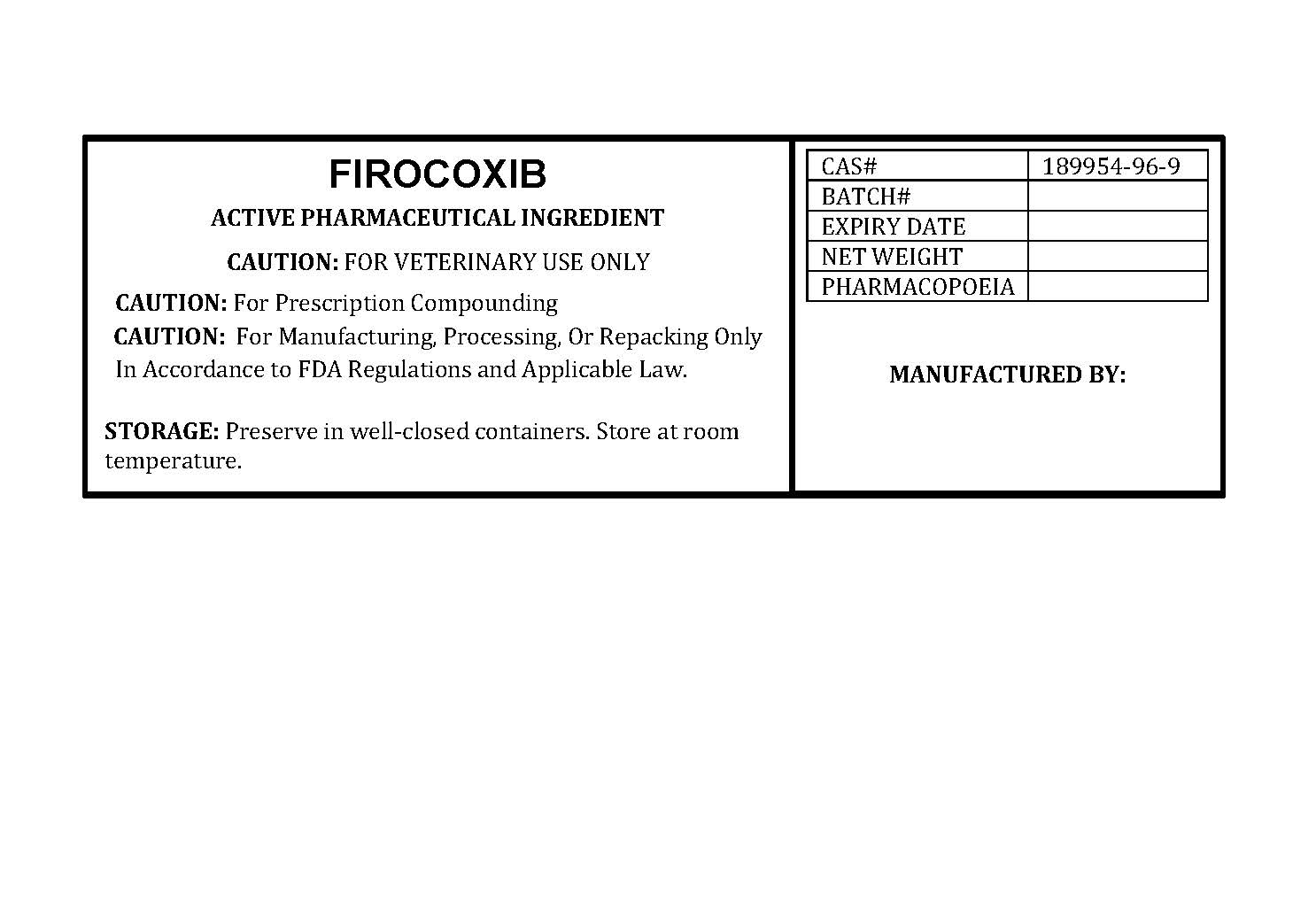 DRUG LABEL: FIROCOXIB
NDC: 86184-104 | Form: POWDER
Manufacturer: MAEDA INC
Category: other | Type: BULK INGREDIENT - ANIMAL DRUG
Date: 20260107

ACTIVE INGREDIENTS: FIROCOXIB 1 g/1 g

FIROCOXIB

PACKAGE LABEL

firocoxiblabelfile.jpg